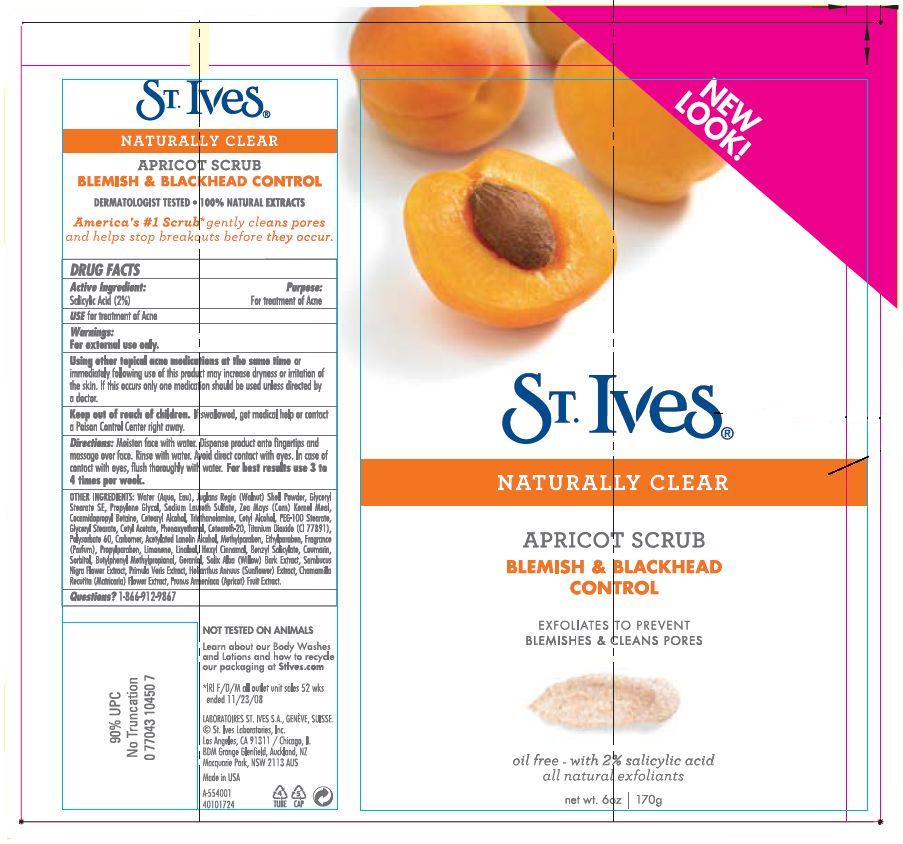 DRUG LABEL: St. Ives Blemish and Blackhead Control
NDC: 12488-0100 | Form: EMULSION
Manufacturer: Alberto Culver USA Inc.
Category: otc | Type: HUMAN OTC DRUG LABEL
Date: 20091216

ACTIVE INGREDIENTS: salicylic acid 0.02 g/1 g
INACTIVE INGREDIENTS: Water; Cocamidopropyl Betaine; methylparaben; propylparaben; cetostearyl alcohol; polysorbate 60; Glyceryl Monostearate; cetyl alcohol; propylene glycol; phenoxyethanol; ethylparaben; trolamine; Primula Veris Extract; sorbitol; Sodium laureth sulfate

St. Ives®
NATURALLY CLEAR
APRICOT SCRUB

DRUG FACTS

Active Ingredient

Salicylic Acid (2%)

Purpose

For treatment of Acne

INDICATIONS AND USAGE

USE for treatment of Acne

Warnings

For external use only.

WHEN USING

Using other topical acne medications at the same time or immediately following use of this product may increase dryness or irritation of the skin. If this occurs only one medication should be used unless directed by a doctor.

Keep out of reach of children. If swallowed, get medical help or contact a Poison Control Center right away.

Directions

Moisten face with water. Dispense product onto fingertips and massage over face. Rinse with water. Avoid direct contact with eyes. In case of contact with eyes, flush thoroughly with water. For best results use 3 to 4 times per week.

OTHER INGREDIENTS

Water (Aqua, Eau), Juglans Regia (Walnut) Shell Powder, Glyceryl Stearate SE, Propylene Glycol, Sodium Laureth Sulfate, Zea Mays (Corn) Kernel Meal, Cocamidopropyl Betaine, Cetearyl Alcohol, Triethanolamine, Cetyl Alcohol, PEG-100 Stearate, Glyceryl Stearate, Cetyl Acetate, Phenoxyethanol, Ceteareth-20, Titanium Dioxide (CI 77891), Polysorbate 60, Carbomer, Acetylated Lanolin Alcohol, Methylparaben, Ethylparaben, Fragrance (Parfum), Propylparaben, Limonene, Linalool, Hexyl Cinnamal, Benzyl Salicylate, Coumarin, Sorbitol, Butylphenyl Methylpropional, Geraniol, Salix Alba (Willow) Bark Extract, Sambucus Nigra Flower Extract, Primula Veris Extract, Helianthus Annuus (Sunflower) Extract, Chamomilla Recutita (Matricaria) Flower Extract, Prunus Armeniaca (Apricot) Fruit Extract.

Questions?

1-866-912-9867

PRINCIPAL DISPLAY PANEL - 170g Tube

NEW
LOOK!

St. Ives®

NATURALLY CLEAR

APRICOT SCRUB

BLEMISH & BLACKHEAD
CONTROL

EXFOLIATES TO PREVENT
BLEMISHES & CLEANS PORES

oil free - with 2% salicylic acid
all natural exfoliants

net wt. 6oz
170g